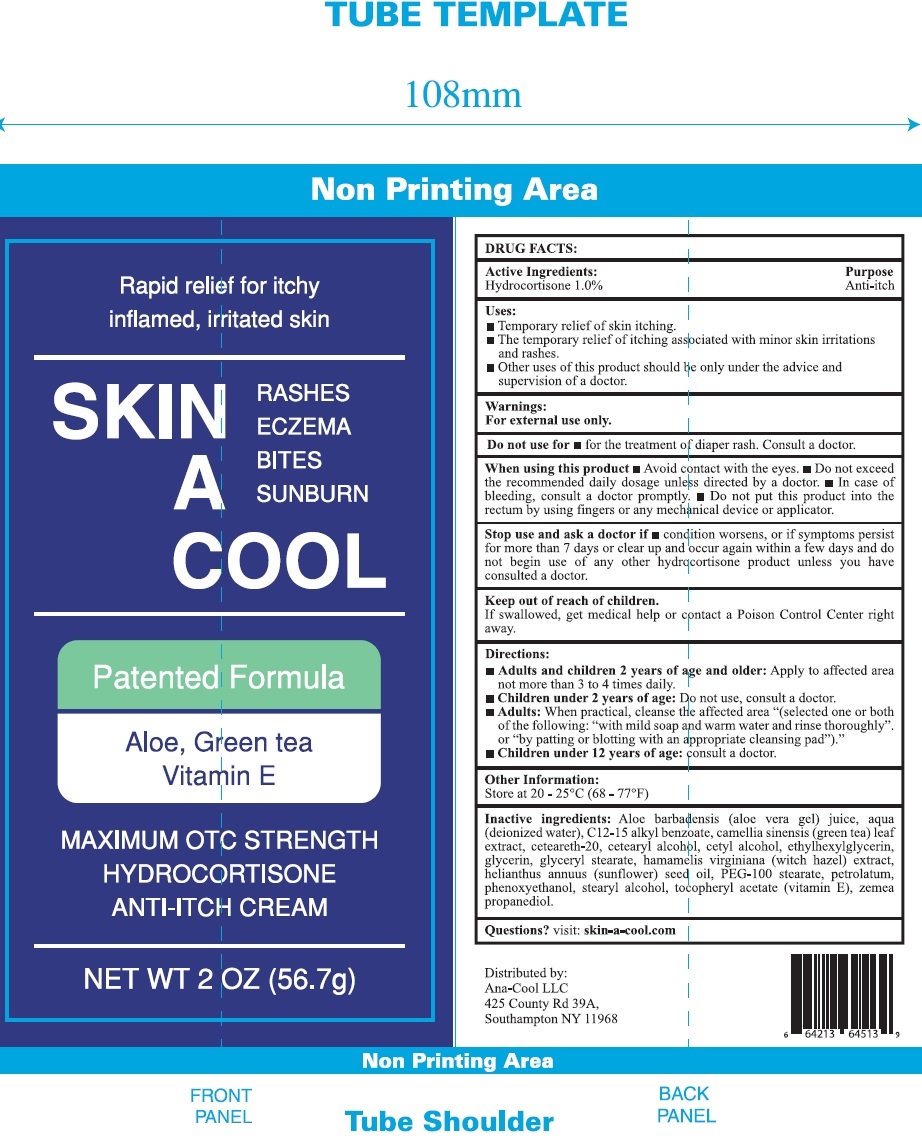 DRUG LABEL: SKIN A COOL Hydrocortisone Anti-Itch
NDC: 70288-173 | Form: CREAM
Manufacturer: Ana-Cool, LLC
Category: otc | Type: HUMAN OTC DRUG LABEL
Date: 20231110

ACTIVE INGREDIENTS: HYDROCORTISONE 10 mg/1 g
INACTIVE INGREDIENTS: ALOE VERA LEAF; WATER; ALKYL (C12-15) BENZOATE; GREEN TEA LEAF; POLYOXYL 20 CETOSTEARYL ETHER; CETOSTEARYL ALCOHOL; CETYL ALCOHOL; ETHYLHEXYLGLYCERIN; GLYCERIN; GLYCERYL MONOSTEARATE; HAMAMELIS VIRGINIANA TOP; SUNFLOWER OIL; PEG-100 STEARATE; PETROLATUM; PHENOXYETHANOL; STEARYL ALCOHOL; .ALPHA.-TOCOPHEROL ACETATE

SKIN A COOL Hydrocortisone Anti-Itch Cream

Active Ingredients:

Hydrocortisone 1.0%

Purpose

Anti-itch

Uses:

- Temporary relief of skin itching.
- The temporary relief of itching associated with minor skin irritations and rashes.
- Other uses of this product should be only under the advise and supervision of a doctor.

Warnings:

For external use only.

Do not use for

- for the treatment of diaper rash. Consult a doctor.

When using this product

- Avoid contact with the eyes.
- Do not exceed the recommended daily dosage unless directed by a doctor.
- In case of bleeding, consult a doctor promptly.
- Do not put this product into the rectum by using fingers or any mechanical device or applicator.

Stop use and ask a doctor if

- condition worsens, or if symptoms persist for more than 7 days or clear up and occur again within a few days and do not begin use of any other hydrocorstisone product unless you have consulted a doctor.

Keep out of reach of children.

If swallowed, get medical help or contact a Poison Control Center right away.

Directions:

Apply to affected area not more than 3 to 4 times daily. Adults and children 2 years of age and older:

Do not use, consult a doctor. Children under 2 years of age:

When practical, cleanse the affected area "(selected one or both of the following: with mild soap and warm water and rinse thoroughly". or "by patting or blotting with an appropriate cleansing pad").: Adults:

consult a doctor. Children under 12 years of age:

Other Information:

Store at 20-25°C (68-77°F)

Inactive ingredients:

Aloe barbadensis (aloe vera gel) juice, aqua (deionized water), C12-15 alkyl benzoate, camellia sinensis (green tea) leaf extract, ceteareth-20, cetearyl alcohol, cetyl alcohol, ethylhexylglycerin, glycerin, glyceryl stearate, hamamelis virginiana (witch hazel) extract, helianthus annuus (sunflower) seed oil, PEG-100 stearate, petrolatum, phenoxyethanol, stearyl alcohol, tocopheryl acetate (vitamin E), zemea propanediol.

Questions?

visit: skin-a-cool.com